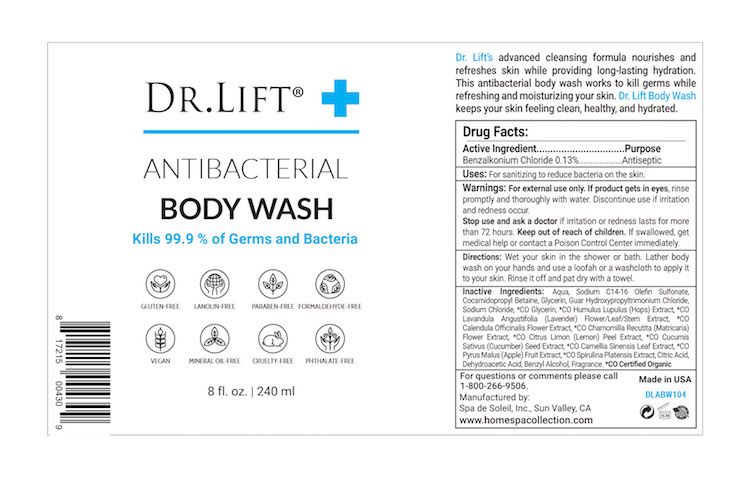 DRUG LABEL: Dr Lift Antibacterial Body Wash
NDC: 68062-2241 | Form: GEL
Manufacturer: Spa de Soleil
Category: otc | Type: HUMAN OTC DRUG LABEL
Date: 20251010

ACTIVE INGREDIENTS: BENZALKONIUM CHLORIDE 0.46 mg/240 mg
INACTIVE INGREDIENTS: COCAMIDOPROPYL BETAINE; WATER; SODIUM CHLORIDE

Dr Lift Antibacterial Body Wash

Active Ingredient

Benzalkonium Chloride 0.13 %

Purpose

Antiseptic

Warnings

For external use only.

When using this product: If in eyes, rinse promptly and thoroughly with water. Discontinue use if irritation or redness develop.

Stop use and ask a doctor if irritation or redness occur for more than 72 hours.

Keep out of reach of children. If swallowed, get medical help or contact a Poison Control Center right away.

Keep out of reach of children.

Directions

Apply to wet skin. Scrub thoroughly. Rinse and dry. Use as needed.

DOSAGE AND ADMINISTRATION

Place enough product in the palm of your hands to thoroughly cover you hands. Rub hands together briskly until product is completely absorbed and hands are dry.

Inactive Ingredients:

Inactive Ingredients

Sodium Chloride, Cocamidopropyl betaine, Aqua, Sodium Laureth Sulfate, Carbomer, Glycerin, *CO Humulus Lupulus (Hops) Extract, *CO Lavandula Angustifolia (Lavender) Flower/Leaf/Stem Extract, *CO Calendula Officinalis Flower Extract, *CO Chamomilla Recutita (Matricaria) Flower Extract, *CO Citrus Limon (Lemon) Peel Extract, *CO Cucumis Sativus (Cucumber) Seed Extract, *CO Camellia Sinensis Leaf Extract, *CO Pyrus Malus (Apple) Fruit Extract, *CO Spirulina Platensis Extract, Xanthan Gum.

*CO Certified Organic